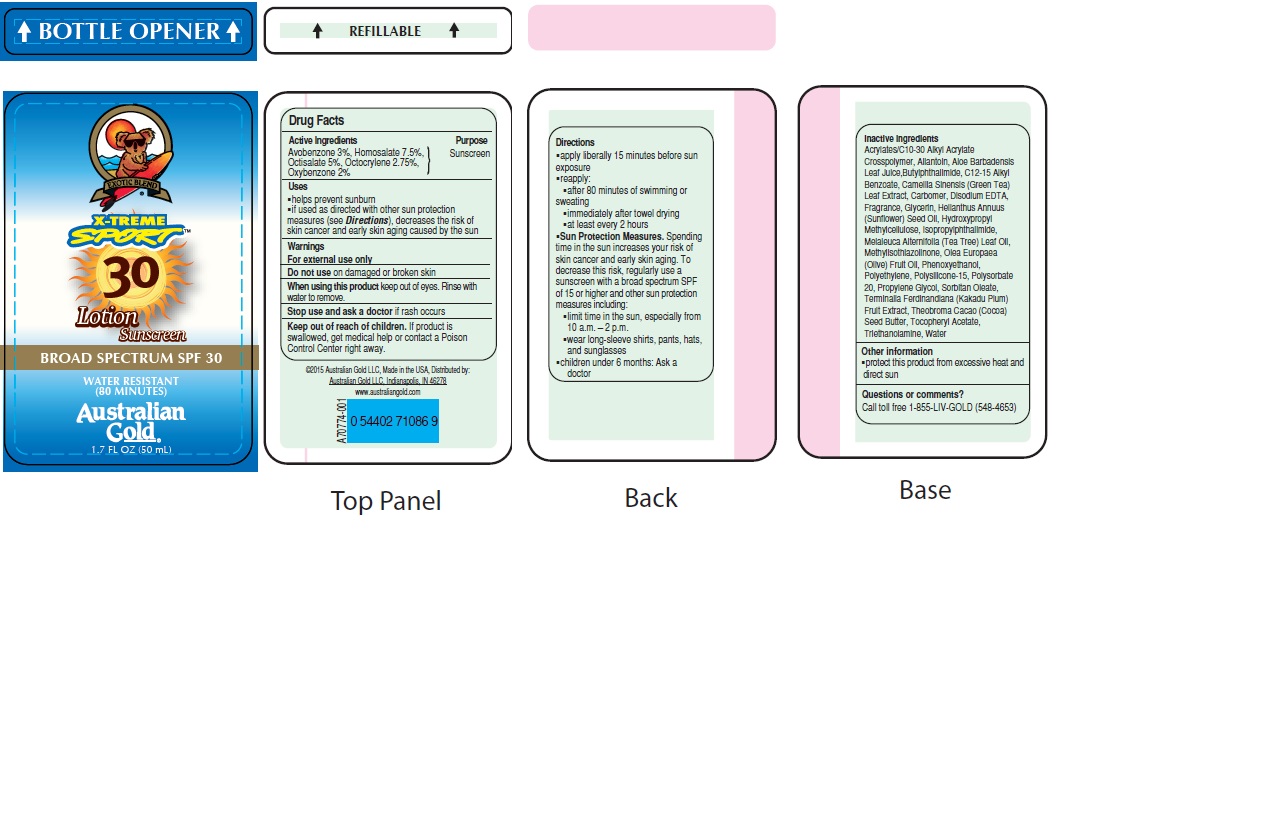 DRUG LABEL: Australian Gold
NDC: 58443-0197 | Form: LOTION
Manufacturer: Prime Enterprises Inc.
Category: otc | Type: HUMAN OTC DRUG LABEL
Date: 20200117

ACTIVE INGREDIENTS: OXYBENZONE 19.8 mg/1 mL; AVOBENZONE 29.7 mg/1 mL; HOMOSALATE 74.3 mg/1 mL; OCTISALATE 49.5 mg/1 mL; OCTOCRYLENE 27.2 mg/1 mL
INACTIVE INGREDIENTS: TEA TREE OIL; COCOA BUTTER; EDETATE DISODIUM; GLYCERIN; SUNFLOWER OIL; METHYLISOTHIAZOLINONE; ISOPROPYLPHTHALIMIDE; HYPROMELLOSES; OLIVE OIL; PHENOXYETHANOL; HIGH DENSITY POLYETHYLENE; POLYSILICONE-15; POLYSORBATE 20; PROPYLENE GLYCOL; SORBITAN MONOOLEATE; CARBOMER HOMOPOLYMER TYPE C (ALLYL PENTAERYTHRITOL CROSSLINKED); GREEN TEA LEAF; ALKYL (C12-15) BENZOATE; N-BUTYLPHTHALIMIDE; ALOE VERA LEAF; ALLANTOIN; (C10-C30)ALKYL METHACRYLATE ESTER; KAKADU PLUM; ALPHA-TOCOPHEROL ACETATE; TROLAMINE; WATER

Australian Gold SPF 30 Broad Spectrum Lotion Sunscreen X-Treme Sport

Active Ingredients

Avobenzone 3%

Homosalate 7.5%

Octisalate 5%

Octocrylene 2.75%

Oxybenzone 2%

PURPOSE

Sunscreen

Uses

- helps prevent sunburn
- if used as directed with other sun protection measures (see Directions), decreases the risk of skin cancer and early skin aging caused by the sun

WARNINGS

For external use only.

Do not use on damaged or broken skin

When using this product keep out of eyes. Rinse with water to remove.

Stop use and ask a doctor if rash occurs

Keep out of reach of children. If product is swallowed, get medical help or contact a Poison Control Center right away.

Directions

- apply liberally 15 minutes before sun exposure
- reapply:
- after 80 minutes of swimming or sweating
- immediately after towel drying
- at least every 2 hours
- Sun Protection Measures. Spending time in the sun increases your risk of skin cancer and early skin aging. To decrease this risk, regularly use a sunscreen with broad spectrum SPF of 15 or higher and other sun protection measures including:
- limit time in the sun, especially from 10 a.m. – 2 p.m.
- wear long-sleeve shirts, pants, hats, and sunglasses
- children under 6 months: Ask a doctor

INACTIVE INGREDIENT

Acrylates/C10-30 Alkyl Acrylate Crosspolymer, Allantoin, Aloe Barbadensis Leaf Juice, Butylphthalimide, C12-15 Alkyl Benzoate, Camellia Sinensis (Green Tea) Leaf Extract, Carbomer, Disodium EDTA, Fragrance, Glycerin, Helianthus Annuus (Sunflower) Seed Oil, Hydroxypropyl Methylcellulose, Isopropylphthalimide, Melaleuca Alternifolia (Tea Tree) Leaf Oil, Methylisothiazolinone, Olea Europaea (Olive) Fruit Oil, Phenoxyethanol, Polyethylene, Polysilicone-15, Polysorbate 20, Propylene Glycol, Sorbitan Oleate, Terminalia Ferdinandiana (Kakadu Plum) Fruit Extract, Theobroma Cacao (Cocoa) Seed Butter, Tocopheryl Acetate, Triethanolamine, Water

Other Information

- protect this product from excesive heat and direct sun

Questions or Comments?

Call toll free 1-855-LIV-GOLD (548-4653)